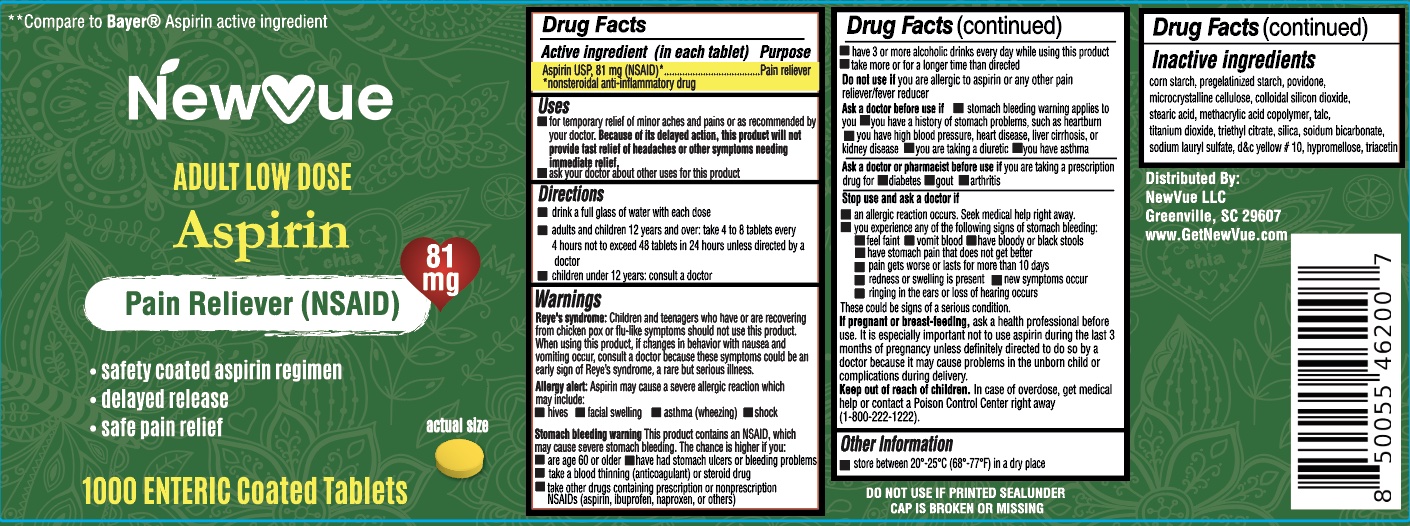 DRUG LABEL: Aspirin 81 mg
NDC: 83813-001 | Form: TABLET, DELAYED RELEASE
Manufacturer: NewVue LLC
Category: otc | Type: HUMAN OTC DRUG LABEL
Date: 20231123

ACTIVE INGREDIENTS: ASPIRIN 81 mg/1 1
INACTIVE INGREDIENTS: TRIACETIN; STEARIC ACID; POVIDONE; TRIETHYL CITRATE; SODIUM LAURYL SULFATE; MICROCRYSTALLINE CELLULOSE 102; STARCH, CORN; SILICON DIOXIDE; METHACRYLIC ACID - ETHYL ACRYLATE COPOLYMER (1:2); TITANIUM DIOXIDE; SODIUM BICARBONATE; TALC; D&C YELLOW NO. 10; HYPROMELLOSE 2910 (6 MPA.S)

Aspirin 81mg Enteric Coated Tablets

INACTIVE INGREDIENT

corn starch, pregelatinized starch, povidone. microcrystalline cellulose, colloidal silicon dioxide, stearic acid, methacrylic acid and ethyl acrylate copolymer, talc, titanium dioxide, triethyl citrate, sodium bicarbonate, sodium lauryl sulfate, d&c yellow #10, hypromellose, triacetin

ACTIVE INGREDIENT

Aspirin 81 mg (NSAID*) *nonsteroidal anti-inflammatory drug

Ask a doctor before use if stomach bleeding warning applies to you you have a history of stomach problems, such as heartburn you have high blood pressure, heart disease, liver cirrhosis, or kidney disease you are taking a diuretic you have asthma you have not been drinking fluids you have lost a lot of fluid due to vomiting or diarrhea

Ask a doctor or pharmacist before use if you are - taking a prescription drug for diabetes, gout, or arthritis - taking any other drug - under a doctor's care for any serious condition

Aspirin Drug Facts

Do not use: if you are allergic to aspirin or any other pain reliver/fever reducer

Keep out of reach of children. In case of overdose, get medical help or contact a Poison Control Center right away.

PREGNANCY OR BREAST FEEDING

If pregnant or breast-feeding, ask a health professional before use. It is especially important not to use aspirin during the last 3 months of pregnancy unless definitely directed to do so by a doctor becwause it may cause problems in the unborn child or complications during delivery.

PURPOSE

Pain reliever

Stop use and ask a doctor if - an allergic reaction occurs. Seek medical help right away. - you are experierance any of the following signs of stomach bleeding: feel faint, have bloody or black stools, vomit blood, have stomach pain that does not get better - pain gets worse or lasts more than 10 days - redness or swelling is present - new symptoms occur - ringing in the ears or a loss of hearing occurs. these could be signs of a serious condition.

DOSAGE AND ADMINISTRATION

Drink a full glass of water with each dose - adults and children 12 years and over: take 4 to 8 tablets every 4 hours not to exceed 48 tablets in 24 hours unless directed by a doctor - children under 12 years: consult a doctor

WARNINGS

Reye's syndrome: Children and teenagers who have or are recoving from chicken pox or flu-like symptoms should not use this product. When using this product, if changes in behavior with nausea and vomiting occur, consult a doctor because these symptoms could be early sign of Reye's syndrome, a rare but serious illness.

Stomach bleeding warning: This product contains an NSAID, which may cause severe stomach bleeding. The chance is higher if you: - are age 60 or older - have had stomach ulcers or bleeding problems - take a blood thinning (anticoagulant) or steriod drug - take other drugs contiaining prescription or nonprescription NSAIDs (aspirin, ibuprofen, naprozen, or others) - have 3 or more alcoholic drinks every day while using this product - take more or for longer time than directed

Allergy Alert: Aspirin may cause a severe allergic reaction which may include: - hives - facial swelling - shock - asthma (wheezing)

INDICATIONS AND USAGE

Pin Reliever

PACKAGE LABEL

NDC 83813-001-01